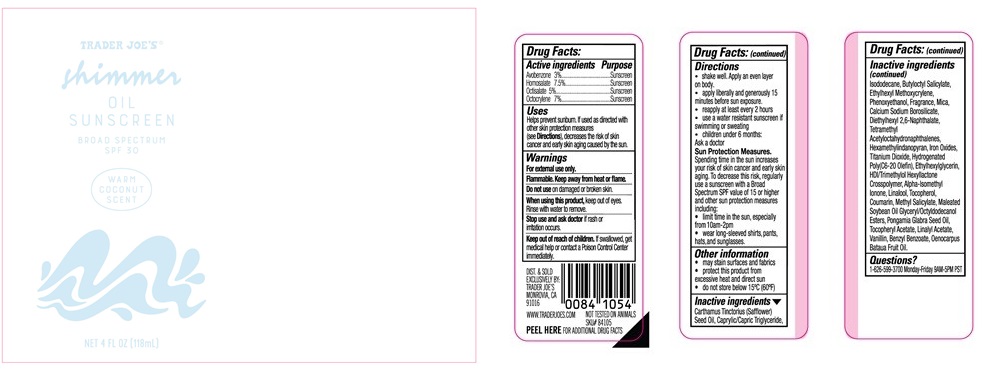 DRUG LABEL: TRADER JOES SHIMMER SUNSCREEN
NDC: 71270-163 | Form: OIL
Manufacturer: Trader Joe's Company
Category: otc | Type: HUMAN OTC DRUG LABEL
Date: 20260209

ACTIVE INGREDIENTS: OCTISALATE 5 g/100 mL; OCTOCRYLENE 7 g/100 mL; AVOBENZONE 3 g/100 mL; HOMOSALATE 7.5 g/100 mL
INACTIVE INGREDIENTS: PONGAMIA GLABRA SEED OIL; MALEATED SOYBEAN OIL GLYCERYL/OCTYLDODECANOL ESTERS; BENZYL BENZOATE; ALPHA-ISOMETHYL IONONE; TOCOPHEROL; OENOCARPUS BATAUA SEED OIL; COUMARIN; ETHYLHEXYLGLYCERIN; HYDROGENATED POLY(C6-20 OLEFIN); HEXAMETHYLINDANOPYRAN; LINALYL ACETATE; HDI/TRIMETHYLOL HEXYLLACTONE CROSSPOLYMER; MICA; ISODODECANE; CAPRYLIC/CAPRIC TRIGLYCERIDE; CARTHAMUS TINCTORIUS (SAFFLOWER) SEED OIL; CALCIUM SODIUM BOROSILICATE; .ALPHA.-TOCOPHEROL ACETATE, D-; METHYL SALICYLATE; FERRIC IRON OXIDE ADIPATE; DIETHYLHEXYL 2,6-NAPHTHALATE; TITANIUM DIOXIDE; TETRAMETHYL ACETYLOCTAHYDRONAPHTHALENES; LINALOOL; PHENOXYETHANOL; ETHYLHEXYL METHOXYCRYLENE; VANILLIN; BUTYLOCTYL SALICYLATE

TRADER JOE’S (as PLD) - Shimmer Oil Sunscreen Broad Spectrum SPF 30 (71270-160)

ACTIVE INGREDIENTS

AVOBENZONE 3%

HOMOSALATE 7.5%

OCTISALATE 5%

OCTOCRYLENE 7%

PURPOSE

Sunscreen

USES

Helps prevent sunburn. If used as directed with other skin protection measures (See Directions), decreases the risk of skin cancer and early skin aging caused by the sun.

WARNINGS

For external use only.

Flammable. Keep away from heat or flame.

Do not use on damaged or broken skin.

When using this product,keep out of eyes. Rinse with water to remove.

Stop use and ask a doctor if rash or irritation occurs.

Keep out of reach of children. If swallowed, get medical help or contact a Poison Control Center immediately.

DIRECTIONS

- Shake well. Apply an even layer on body.
- Apply liberally and generously 15 minutes before sun exposure.
- Reapply at least every 2 hours.
- Use a water resistant sunscreen if swimming or sweating.
- Children under six months of age: Ask a doctor

Sun Protection Measures.Spending time in the sun increases your risk of skin cancer and early skin aging. To decrease this risk, regularly use a sunscreen with a Broad Spectrum SPF 15 value or higher along with other sun protection measures including:

- limit time in the sun, especially from 10 a.m. – 2 p.m.
- wear long-sleeved shirts, pants, hats and sunglasses.

INACTIVE INGREDIENTS

Carthamus Tinctorius (Safflower) Seed Oil, Caprylic/Capric Triglyceride, Isododecane, Butyloctyl Salicylate, Ethylhexyl Methoxycrylene, Phenoxyethanol, Fragrance, Mica, Calcium Sodium Borosilicate, Diethylhexyl 2,6-Naphthalate, Tetramethyl Acetyloctahydronaphthalenes, Hexamethylindanopyran, Iron Oxides, Titanium Dioxide, Hydrogenated Poly(C6-20 Olefin), Ethylhexylglycerin, HDI/Trimethylol Hexyllactone Crosspolymer, Alpha-Isomethyl Ionone, Linalool, Tocopherol, Coumarin, Methyl Salicylate, Maleated Soybean Oil Glyceryl/Octyldodecanol Esters, Pongamia Glabra Seed Oil, Tocopheryl Acetate, Linalyl Acetate, Vanillin, Benzyl Benzoate, Oenocarpus Bataua Fruit Oil.

QUESTIONS?

1- 626-599-3700

Monday – Friday 9 AM – 5 PM PST